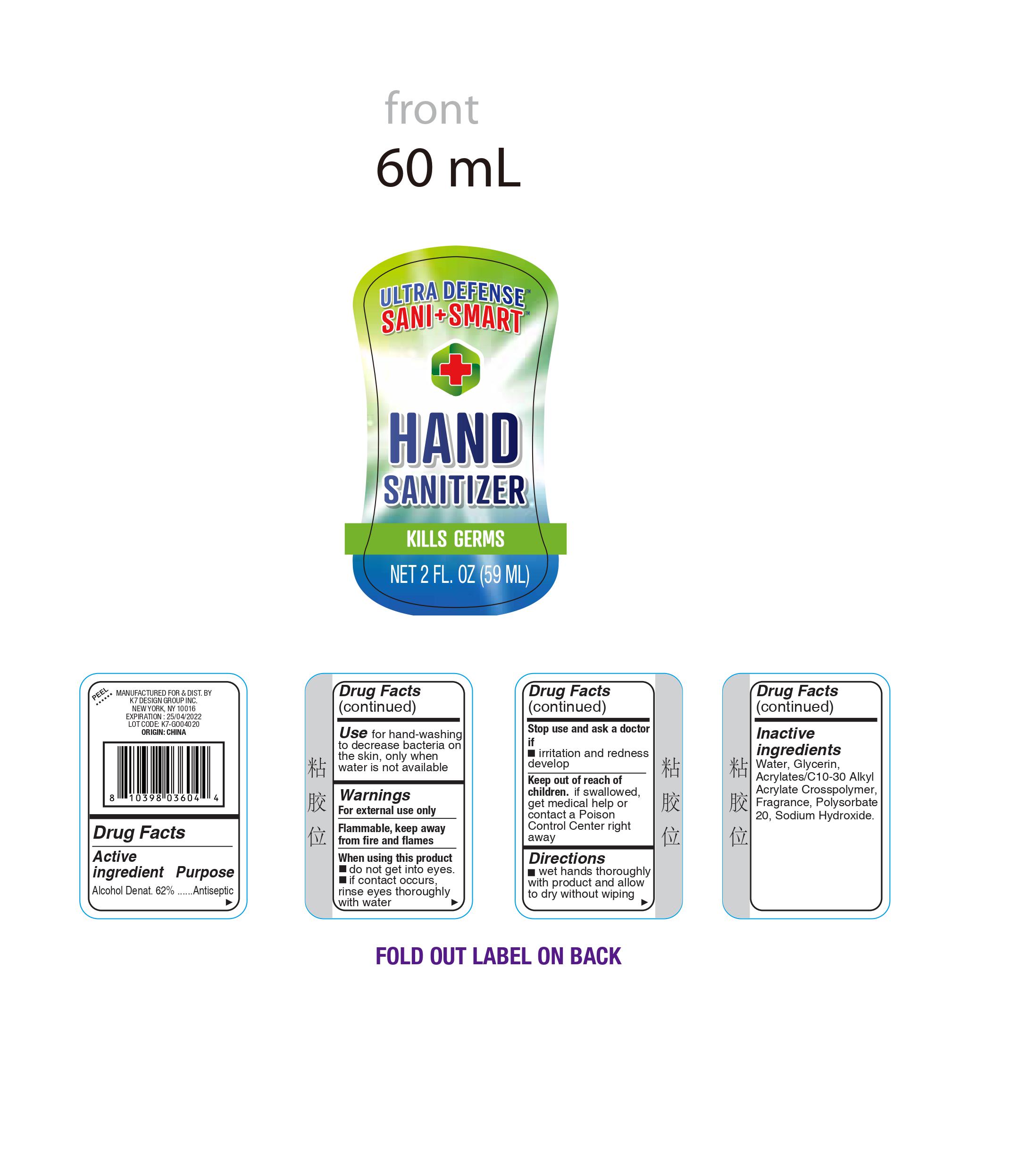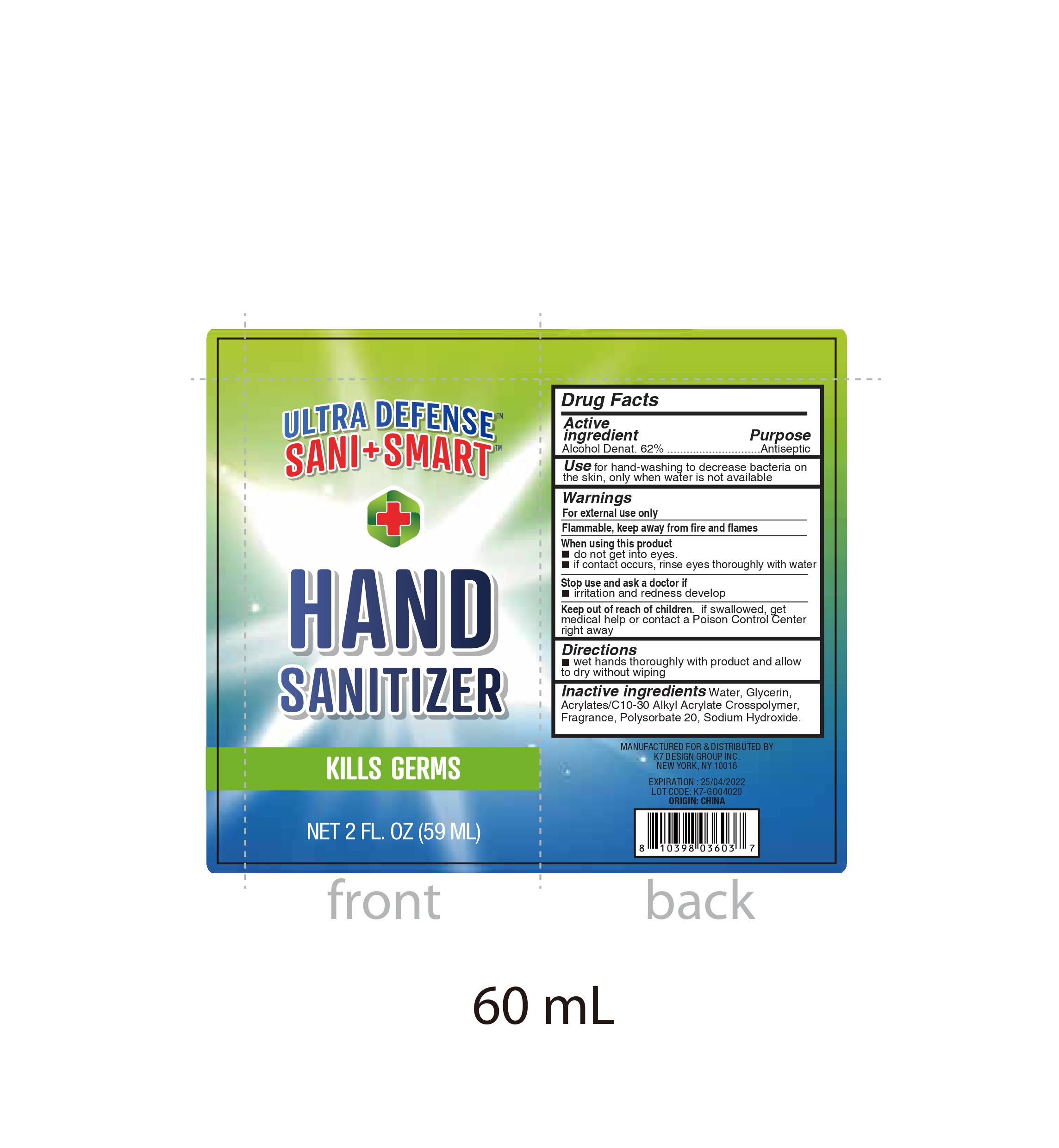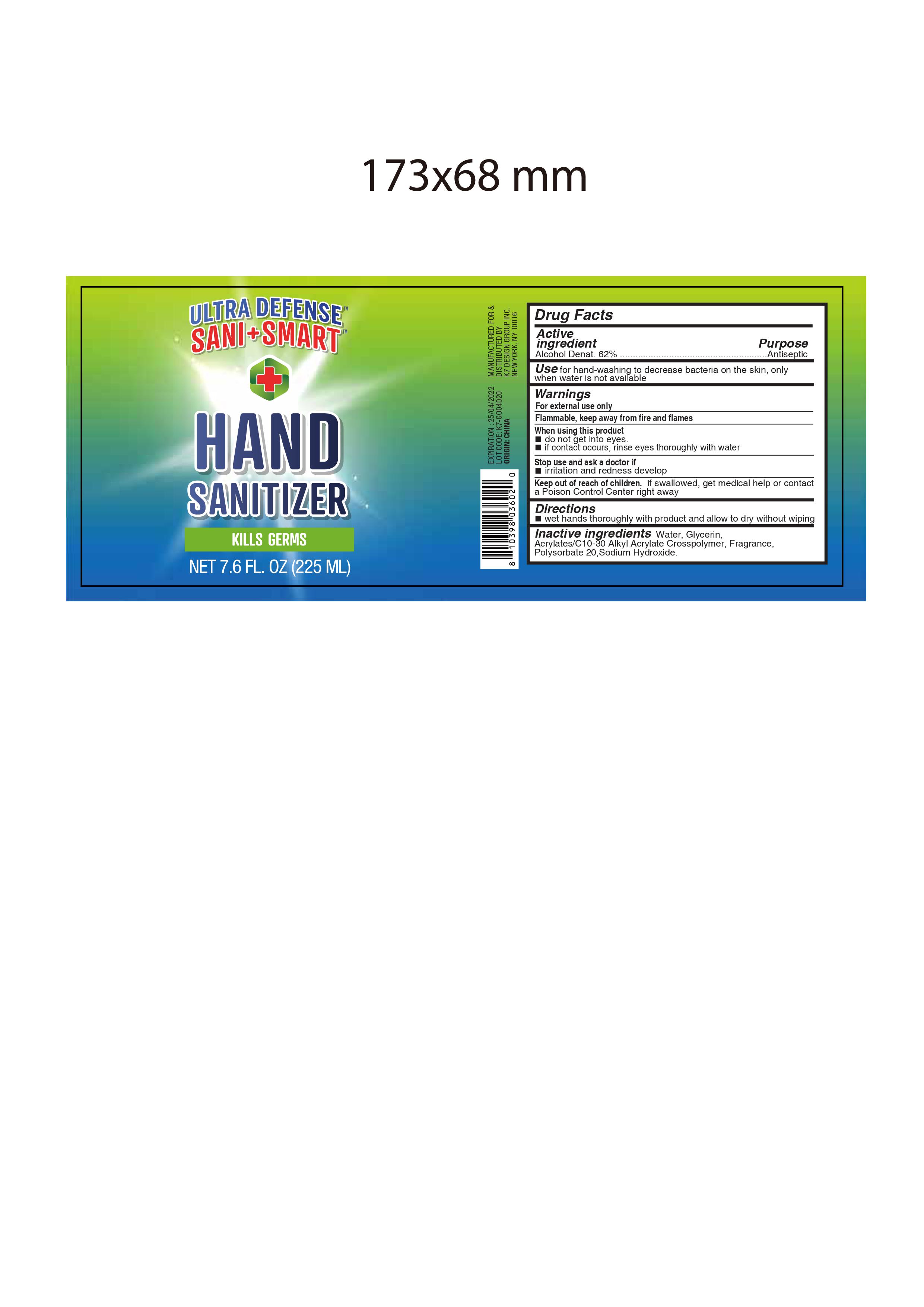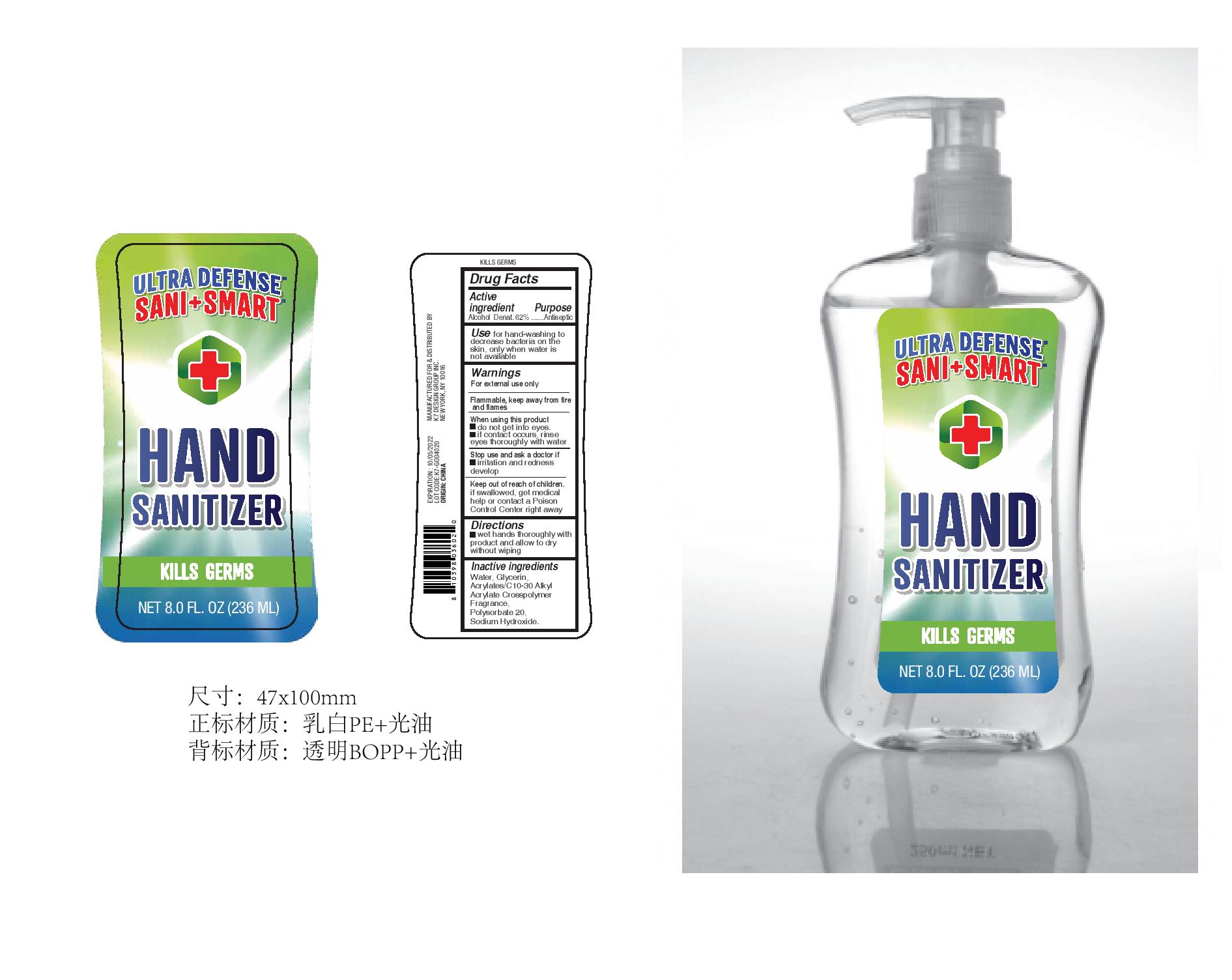 DRUG LABEL: Ultra Defense Sani Smart Hand Sanitizer
NDC: 51522-004 | Form: GEL
Manufacturer: Gold Orient International Limited
Category: otc | Type: HUMAN OTC DRUG LABEL
Date: 20200427

ACTIVE INGREDIENTS: ALCOHOL 65 mL/100 mL
INACTIVE INGREDIENTS: WATER 33 mL/100 mL; POLYSORBATE 20; CARBOMER COPOLYMER TYPE A (ALLYL PENTAERYTHRITOL CROSSLINKED); GLYCERIN; SODIUM HYDROXIDE

Ultra Defense Sani Smart Hand Sanitizer

INDICATIONS AND USAGE

for hand washing to decrease bacteria on the skin only when water is not available.

Drug Facts Active Ingredients

Ethyl Alcohol 65%

Purpose

Antiseptic

DOSAGE AND ADMINISTRATION

- wet hands thoroughly with product and allow to dry without wiping

Inactive Ingredients:

Water(Aqua), Glycerin, Acrylates/C10-30 Alkyl Acrylate Crosspolymer, Polysorbate 20, Sodium Hydroxide, Fragrance (Parfum)

Warning

- For External Use Only.
- Flammable, keep away from fire and flames

Keep out of reach of children.

When using this product

- do not get into eyes.
- if contact occurs, rinse eyes thoroughly with water

Stop us and ask a doctor if

- irritation and redness develop

Keep out of reach of children, if swallowed, get medical help or contact a Poison Control Center right away.